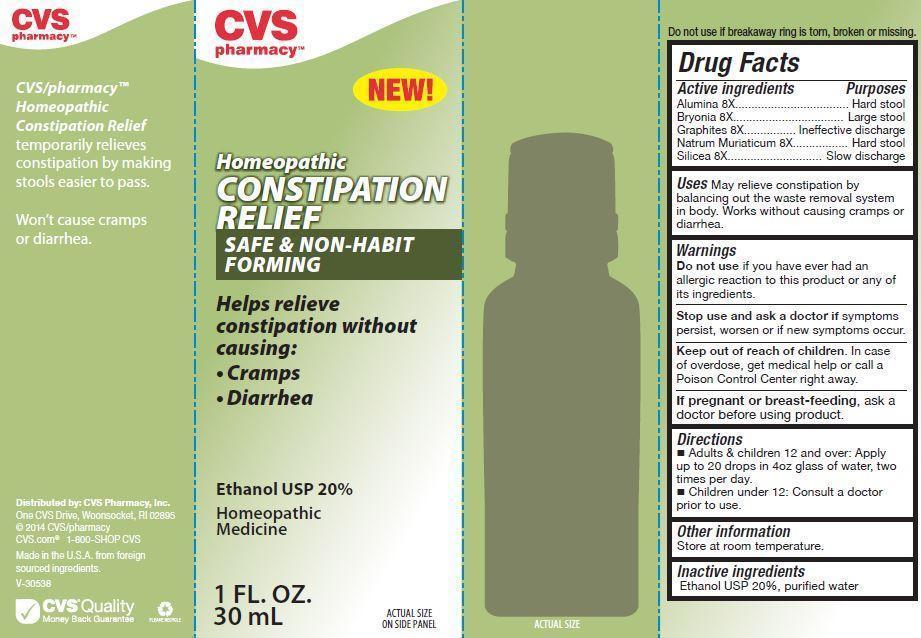 DRUG LABEL: Constipation Relief
NDC: 59779-857 | Form: LIQUID
Manufacturer: WOONSOCKET PRESCR CTR INC
Category: homeopathic | Type: HUMAN OTC DRUG LABEL
Date: 20141030

ACTIVE INGREDIENTS: ALUMINUM OXIDE 8 [hp_X]/30 mL; BRYONIA ALBA ROOT 8 [hp_X]/30 mL; GRAPHITE 8 [hp_X]/30 mL; SODIUM CHLORIDE 8 [hp_X]/30 mL; SILICON DIOXIDE 8 [hp_X]/30 mL
INACTIVE INGREDIENTS: ALCOHOL; WATER

Active Ingredients Purposes

Alumina 8X .......................................... Hard Stool

Bryonia 8X .......................................... Large Stool

Graphites 8X ......................... Ineffective Discharge

Natrum Muriaticum 8X ......................... Hard Stool

Silicea 8X ...................................... Slow Discharge

Uses

May relieve constipation by balancing out the waste removal system in body. Works without causing cramps or diarrhea.

Keep out of reach of children. In case of overdose, get medical help or call a Poison Control Center right away.

Directions

- Adults & children 12 and over: Apply up to 20 drops in 4oz glass of water, two times per day.
- Children under 12: consult a doctor prior to use.

INDICATIONS AND USAGE

Homeopathic

CONSTIPATION RELIEF

SAFE & NON-HABIT FORMING

Helps relieve constipation without causing:

Cramps

Diarrhea

Ethanol USP 20%

Homeopathic Medicine

1 FL. Oz.

30 mL

Warnings

Do not use if you have ever had an allergic reaction to this product or any of its ingredients.

Stop use and ask a doctor if symptoms persist, worsen or if new symptoms occur.

If pregnant or breast-feeding, ask a doctor before using product.

Inactive Ingredients

Ethanol USP 20%, purified water